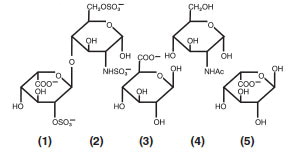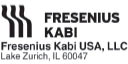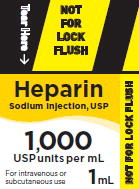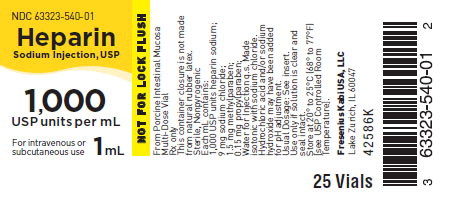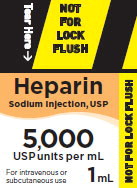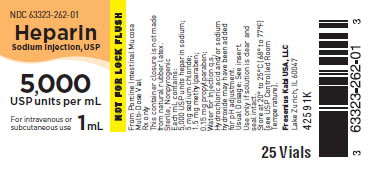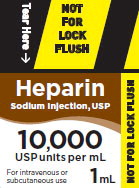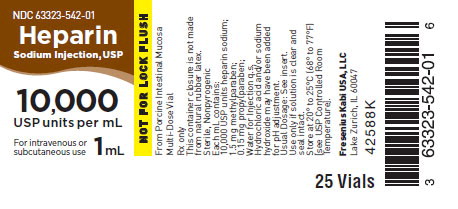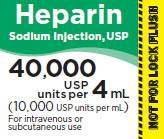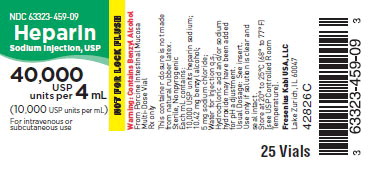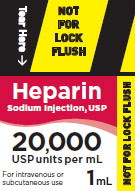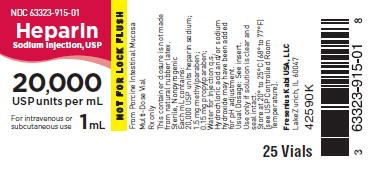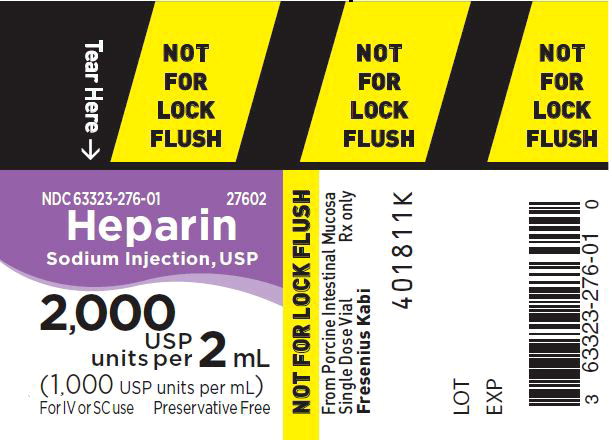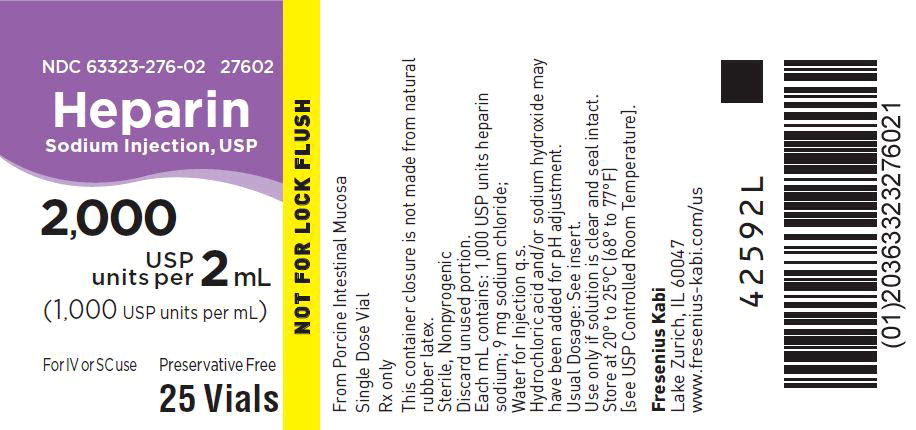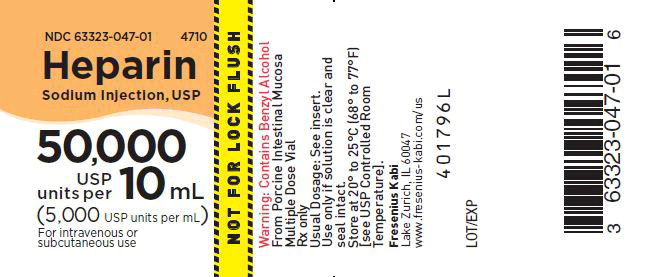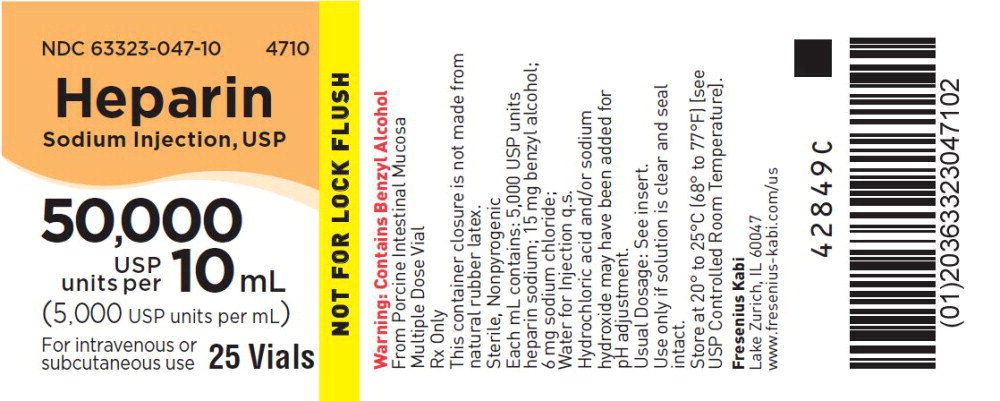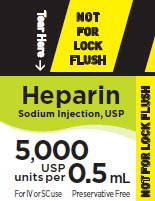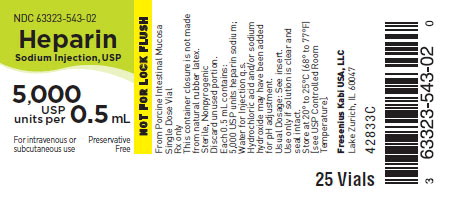 DRUG LABEL: Heparin Sodium
NDC: 63323-542 | Form: INJECTION, SOLUTION
Manufacturer: Fresenius Kabi USA, LLC
Category: prescription | Type: HUMAN PRESCRIPTION DRUG LABEL
Date: 20251128

ACTIVE INGREDIENTS: HEPARIN SODIUM 10000 [USP'U]/1 mL
INACTIVE INGREDIENTS: METHYLPARABEN 1.5 mg/1 mL; PROPYLPARABEN 0.15 mg/1 mL; HYDROCHLORIC ACID; SODIUM HYDROXIDE

Heparin Sodium Injection USP

Rx only

DERIVED FROM PORCINE INTESTINAL MUCOSA.

Available as: Preservative Free or Contains Benzyl Alcohol or Parabens

DESCRIPTION

Heparin is a heterogeneous group of straight-chain anionic mucopolysaccharides, called glycosaminoglycans, having anticoagulant properties. Although others may be present, the main sugars occurring in heparin are: (1) α-L-iduronic acid 2-sulfate, (2) 2-deoxy-2-sulfamino-α-D-glucose 6-sulfate, (3) ß-D-glucuronic acid, (4) 2-acetamido-2-deoxy-α-D-glucose and (5) α-L-iduronic acid. These sugars are present in decreasing amounts, usually in the order (2)> (1)> (4)> (3)> (5), and are joined by glycosidic linkages, forming polymers of varying sizes. Heparin is strongly acidic because of its content of covalently linked sulfate and carboxylic acid groups. In heparin sodium, the acidic protons of the sulfate units are partially replaced by sodium ions.

Heparin Sodium Injection, USP is a sterile solution of heparin sodium derived from porcine intestinal mucosa, standardized for anticoagulant activity, in water for injection. It is to be administered by intravenous or deep subcutaneous routes. The potency is determined by a biological assay using a USP reference standard based on units of heparin activity per milligram.

Structure of Heparin Sodium (representative subunits):

Heparin Sodium Injection, USP (porcine), preservative free, is available as follows:

Each mL of the 1,000 units per mL preparation contains: 1,000 USP Heparin units (porcine); 9 mg sodium chloride; Water for Injection q.s. Made isotonic with sodium chloride. Hydrochloric acid and/or sodium hydroxide may have been added for pH adjustment (5.0 to 7.5).

Each 0.5 mL of the 5,000 units per 0.5 mL preparation contains: 5,000 USP Heparin units (porcine); Water for Injection q.s. Hydrochloric acid and/or sodium hydroxide may have been added for pH adjustment (5.0 to 7.5).

Heparin Sodium Injection, USP (porcine), preserved with benzyl alcohol, is available as follows:

Each mL of the 5,000 units per mL preparation contains: 5,000 USP Heparin units (porcine); 6 mg sodium chloride; 15 mg benzyl alcohol (as a preservative); Water for Injection q.s. Hydrochloric acid and/or sodium hydroxide may have been added for pH adjustment (5.0 to 7.5).

Each mL of the 10,000 units per mL preparation contains: 10,000 USP Heparin units (porcine); 5 mg sodium chloride; 10.42 mg benzyl alcohol (as a preservative); Water for Injection q.s. Hydrochloric acid and/or sodium hydroxide may have been added for pH adjustment (5.0 to 7.5).

Heparin Sodium Injection, USP (porcine), preserved with parabens, is available as follows:

Each mL of the 1,000 units per mL preparation contains: 1,000 USP Heparin units (porcine); 9 mg sodium chloride; 1.5 mg methylparaben; 0.15 mg propylparaben; Water for Injection q.s. Made isotonic with sodium chloride. Hydrochloric acid and/or sodium hydroxide may have been added for pH adjustment (5.0 to 7.5).

Each mL of the 5,000 units per mL preparation contains: 5,000 USP Heparin units (porcine); 5 mg sodium chloride; 1.5 mg methylparaben; 0.15 mg propylparaben; Water for Injection q.s. Hydrochloric acid and/or sodium hydroxide may have been added for pH adjustment (5.0 to 7.5).

Each mL of the 10,000 units per mL preparation contains: 10,000 USP Heparin units (porcine); 1.5 mg methylparaben; 0.15 mg propylparaben; Water for Injection q.s. Hydrochloric acid and/or sodium hydroxide may have been added for pH adjustment (5.0 to 7.5).

Each mL of the 20,000 units per mL preparation contains: 20,000 USP Heparin units (porcine); 1.5 mg methylparaben; 0.15 mg propylparaben; Water for Injection q.s. Hydrochloric acid and/or sodium hydroxide may have been added for pH adjustment (5.0 to 7.5).

CLINICAL PHARMACOLOGY

Heparin inhibits reactions that lead to the clotting of blood and the formation of fibrin clots both in vitro and in vivo. Heparin acts at multiple sites in the normal coagulation system. Small amounts of heparin in combination with antithrombin III (heparin cofactor) can inhibit thrombosis by inactivating activated Factor X and inhibiting the conversion of prothrombin to thrombin. Once active thrombosis has developed, larger amounts of heparin can inhibit further coagulation by inactivating thrombin and preventing the conversion of fibrinogen to fibrin. Heparin also prevents the formation of a stable fibrin clot by inhibiting the activation of the fibrin stabilizing factor.

Bleeding time is usually unaffected by heparin. Clotting time is prolonged by full therapeutic doses of heparin; in most cases, it is not measurably affected by low doses of heparin.

Patients over 60 years of age, following similar doses of heparin, may have higher plasma levels of heparin and longer activated partial thromboplastin times (APTTs) compared with patients under 60 years of age.

Peak plasma levels of heparin are achieved two to four hours following subcutaneous administration, although there are considerable individual variations. Loglinear plots of heparin plasma concentrations with time, for a wide range of dose levels, are linear, which suggests the absence of zero order processes. Liver and the reticuloendothelial system are the sites of biotransformation. The biphasic elimination curve, a rapidly declining alpha phase (t 1⁄2 = 10 minutes) and after the age of 40 a slower beta phase, indicates uptake in organs. The absence of a relationship between anticoagulant half-life and concentration half-life may reflect factors such as protein binding of heparin.

Heparin does not have fibrinolytic activity; therefore, it will not lyse existing clots.

INDICATIONS AND USAGE

Heparin Sodium Injection is indicated for:

Anticoagulant therapy in prophylaxis and treatment of venous thrombosis and its extension;

Low-dose regimen for prevention of postoperative deep venous thrombosis and pulmonary embolism in patients undergoing major abdominothoracic surgery or who, for other reasons, are at risk of developing thromboembolic disease (see DOSAGE AND ADMINISTRATION);

Prophylaxis and treatment of pulmonary embolism;

Atrial fibrillation with embolization;

Treatment of acute and chronic consumptive coagulopathies (disseminated intravascular coagulation);

Prevention of clotting in arterial and cardiac surgery;

Prophylaxis and treatment of peripheral arterial embolism.

Heparin may also be employed as an anticoagulant in blood transfusions, extracorporeal circulation, and dialysis procedures.

CONTRAINDICATIONS

Heparin sodium should NOT be used in patients with the following conditions:

Severe thrombocytopenia;

When suitable blood coagulation tests, e.g., the whole blood clotting time, partial thromboplastin time, etc., cannot be performed at appropriate intervals (this contraindication refers to full-dose heparin; there is usually no need to monitor coagulation parameters in patients receiving low-dose heparin);

An uncontrollable active bleeding state (see WARNINGS), except when this is due to disseminated intravascular coagulation.

WARNINGS

Heparin is not intended for intramuscular use.

Fatal Medication Errors

Do not use Heparin Sodium Injection as a “catheter lock flush” product. Heparin Sodium Injection is supplied in vials containing various strengths of heparin, including vials that contain a highly concentrated solution of 10,000 units in 1 mL. Fatal hemorrhages have occurred in pediatric patients due to medication errors in which 1 mL Heparin Sodium Injection vials were confused with 1 mL “catheter lock flush” vials. Carefully examine all Heparin Sodium Injection vials to confirm the correct vial choice prior to administration of the drug.

Benzyl Alcohol Toxicity

Use preservative-free HEPARIN SODIUM INJECTION in neonates and infants. The preservative benzyl alcohol has been associated with serious adverse events and death in pediatric patients. The minimum amount of benzyl alcohol at which toxicity may occur is not known. Premature and low-birth weight infants may be more likely to develop toxicity (see PRECAUTIONS, Pediatric Use).

Hypersensitivity

Patients with documented hypersensitivity to heparin should be given the drug only in clearly life-threatening situations (see ADVERSE REACTIONS, Hypersensitivity).

Hemorrhage

Hemorrhage can occur at virtually any site in patients receiving heparin. An unexplained fall in hematocrit, fall in blood pressure or any other unexplained symptom should lead to serious consideration of a hemorrhagic event.

Heparin sodium should be used with extreme caution in disease states in which there is increased danger of hemorrhage. Some of the conditions in which increased danger of hemorrhage exists are:

Cardiovascular—Subacute bacterial endocarditis, severe hypertension.

Surgical—During and immediately following (a) spinal tap or spinal anesthesia or (b) major surgery, especially involving the brain, spinal cord, or eye.

Hematologic—Conditions associated with increased bleeding tendencies, such as hemophilia, thrombocytopenia and some vascular purpuras.

Gastrointestinal—Ulcerative lesions and continuous tube drainage of the stomach or small intestine.

Other—Menstruation, liver disease with impaired hemostasis.

Coagulation Testing

When heparin sodium is administered in therapeutic amounts, its dosage should be regulated by frequent blood coagulation tests. If the coagulation test is unduly prolonged or if hemorrhage occurs, heparin sodium should be promptly discontinued (see OVERDOSAGE).

Thrombocytopenia

Thrombocytopenia has been reported to occur in patients receiving heparin with a reported incidence of up to 30%. Platelet counts should be obtained at baseline and periodically during heparin administration. Mild thrombocytopenia (count greater than 100,000/mm ^3) may remain stable or reverse even if heparin is continued. However, thrombocytopenia of any degree should be monitored closely. If the count falls below 100,000/mm ^3 or if recurrent thrombosis develops (see Heparin-induced Thrombocytopenia and Heparin-induced Thrombocytopenia and Thrombosis), the heparin product should be discontinued, and, if necessary, an alternative anticoagulant administered.

Heparin-induced Thrombocytopenia (HIT) and Heparin-induced Thrombocytopenia and Thrombosis (HITT)

Heparin-induced Thrombocytopenia (HIT) is a serious antibody-mediated reaction resulting from irreversible aggregation of platelets. HIT may progress to the development of venous and arterial thromboses, a condition referred to as Heparin-induced Thrombocytopenia and Thrombosis (HITT). Thrombotic events may also be the initial presentation for HITT. These serious thromboembolic events include deep vein thrombosis, pulmonary embolism, cerebral vein thrombosis, limb ischemia, stroke, myocardial infarction, mesenteric thrombosis, renal arterial thrombosis, skin necrosis, gangrene of the extremities that may lead to amputation, and possibly death. Thrombocytopenia of any degree should be monitored closely. If the platelet count falls below 100,000/mm ^3 or if recurrent thrombosis develops, the heparin product should be promptly discontinued and alternative anticoagulants considered, if patients require continued anticoagulation.

Delayed Onset of HIT and HITT

Heparin-induced Thrombocytopenia and Heparin-induced Thrombocytopenia and Thrombosis can occur up to several weeks after the discontinuation of heparin therapy. Patients presenting with thrombocytopenia or thrombosis after discontinuation of heparin should be evaluated for HIT and HITT.

PRECAUTIONS

General

Thrombocytopenia, Heparin-induced Thrombocytopenia (HIT) and Heparin-induced Thrombocytopenia and Thrombosis (HITT)

See WARNINGS.

Heparin Resistance—Increased resistance to heparin is frequently encountered in fever, thrombosis, thrombophlebitis, infections with thrombosing tendencies, myocardial infarction, cancer and in postsurgical patients.

Increased Risk to Older Patients, Especially Women—A higher incidence of bleeding has been reported in patients, particularly women, over 60 years of age.

Laboratory Tests

Periodic platelet counts, hematocrits, and tests for occult blood in stool are recommended during the entire course of heparin therapy, regardless of the route of administration (see DOSAGE AND ADMINISTRATION).

Drug Interactions

Oral Anticoagulants—Heparin sodium may prolong the one-stage prothrombin time. Therefore, when heparin sodium is given with dicumarol or warfarin sodium, a period of at least five hours after the last intravenous dose or 24 hours after the last subcutaneous dose should elapse before blood is drawn, if a valid prothrombin time is to be obtained.

Platelet Inhibitors—Drugs such as acetylsalicylic acid, dextran, phenylbutazone, ibuprofen, indomethacin, dipyridamole, hydroxychloroquine and others that interfere with platelet- aggregation reactions (the main hemostatic defense of heparinized patients) may induce bleeding and should be used with caution in patients receiving heparin sodium.

Other Interactions—Digitalis, tetracyclines, nicotine or antihistamines may partially counteract the anticoagulant action of heparin sodium. Intravenous nitroglycerin administered to heparinized patients may result in a decrease of the partial thromboplastin time with subsequent rebound effect upon discontinuation of nitroglycerin. Careful monitoring of partial thromboplastin time and adjustment of heparin dosage are recommended during coadministration of heparin and intravenous nitroglycerin.

Drug/Laboratory Tests Interactions

Hyperaminotransferasemia—Significant elevations of aminotransferase (SGOT [S-AST] and SGPT [S-ALT]) levels have occurred in a high percentage of patients (and healthy subjects) who have received heparin. Since aminotransferase determinations are important in the differential diagnosis of myocardial infarction, liver disease and pulmonary emboli, increases that might be caused by drugs (like heparin) should be interpreted with caution.

Carcinogenesis, Mutagenesis, Impairment of Fertility

No long-term studies in animals have been performed to evaluate carcinogenic potential of heparin. Also, no reproduction studies in animals have been performed concerning mutagenesis or impairment of fertility.

Pregnancy

Pregnancy Category C

There are no adequate and well-controlled studies on heparin use in pregnant women. In published reports, heparin exposure during pregnancy did not show evidence of an increased risk of adverse maternal or fetal outcomes in humans. Heparin sodium does not cross the placenta, based on human and animal studies. Administration of heparin to pregnant animals at doses higher than the maximum human daily dose based on body weight resulted in increased resorptions. Use heparin sodium during pregnancy only if the potential benefit justifies the potential risk to the fetus.

If available, preservative-free Heparin Sodium Injection is recommended when heparin therapy is needed during pregnancy. There are no known adverse outcomes associated with fetal exposure to the preservative benzyl alcohol through maternal drug administration; however, the preservative benzyl alcohol can cause serious adverse events and death when administered intravenously to neonates and infants (see PRECAUTIONS, Pediatric Use).

In a published study conducted in rats and rabbits, pregnant animals received heparin intravenously during organogenesis at a dose of 10,000 units/kg/day, approximately 10 times the maximum human daily dose based on body weight. The number of early resorptions increased in both species. There was no evidence of teratogenic effects.

Nursing Mothers

If available, preservative-free HEPARIN SODIUM INJECTION is recommended when heparin therapy is needed during lactation. Due to its large molecular weight, heparin is not likely to be excreted in human milk, and any heparin in milk would not be orally absorbed by a nursing infant. Benzyl alcohol present in maternal serum is likely to cross into human milk and may be orally absorbed by a nursing infant. Exercise caution when administering HEPARIN SODIUM INJECTION to a nursing mother (see PRECAUTIONS, Pediatric Use).

Pediatric Use

There are no adequate and well-controlled studies on heparin use in pediatric patients. Pediatric dosing recommendations are based on clinical experience (see DOSAGE AND ADMINISTRATION, Pediatric Use).

Carefully examine all Heparin Sodium Injection vials to confirm choice of the correct strength prior to administration of the drug. Pediatric patients, including neonates, have died as a result of medication errors in which HEPARIN SODIUM INJECTION vials have been confused with “catheter lock flush” vials (see WARNINGS, Fatal Medication Errors).

Benzyl Alcohol Toxicity

Use preservative-free Heparin Sodium Injection in neonates and infants. The preservative benzyl alcohol has been associated with serious adverse events and death in pediatric patients. The “gasping syndrome” (characterized by central nervous system depression, metabolic acidosis, gasping respirations, and high levels of benzyl alcohol and its metabolites found in the blood and urine) has been associated with benzyl alcohol dosages >99 mg/kg/day in neonates and low-birth weight infants. Additional symptoms may include gradual neurological deterioration, seizures, intracranial hemorrhage, hematologic abnormalities, skin breakdown, hepatic and renal failure, hypotension, bradycardia, and cardiovascular collapse.

Although normal therapeutic doses of this product deliver amounts of benzyl alcohol that are substantially lower than those reported in association with the “gasping syndrome”, the minimum amount of benzyl alcohol at which toxicity may occur is not known. Premature and low-birth weight infants may be more likely to develop toxicity. Practitioners administering this and other medications containing benzyl alcohol should consider the combined daily metabolic load of benzyl alcohol from all sources.

Geriatric Use

A higher incidence of bleeding has been reported in patients over 60 years of age, especially women (see PRECAUTIONS, General). Clinical studies indicate that lower doses of heparin may be indicated in these patients (see CLINICAL PHARMACOLOGY and DOSAGE AND ADMINISTRATION).

ADVERSE REACTIONS

Hemorrhage

Hemorrhage is the chief complication that may result from heparin therapy (see WARNINGS). An overly prolonged clotting time or minor bleeding during therapy can usually be controlled by withdrawing the drug (see OVERDOSAGE). It should be appreciated that gastrointestinal or urinary tract bleeding during anticoagulant therapy may indicate the presence of an underlying occult lesion. Bleeding can occur at any site but certain specific hemorrhagic complications may be difficult to detect:

(a) Adrenal hemorrhage, with resultant acute adrenal insufficiency, has occurred during anticoagulant therapy. Therefore, such treatment should be discontinued in patients who develop signs and symptoms of acute adrenal hemorrhage and insufficiency. Initiation of corrective therapy should not depend on laboratory confirmation of the diagnosis, since any delay in an acute situation may result in the patient’s death.

(b) Ovarian (corpus luteum) hemorrhage developed in a number of women of reproductive age receiving short- or long-term anticoagulant therapy. This complication, if unrecognized, may be fatal.

(c) Retroperitoneal hemorrhage.

Thrombocytopenia, Heparin-induced Thrombocytopenia (HIT) and Heparin-induced Thrombocytopenia and Thrombosis (HITT) and Delayed Onset of HIT and HITT

See WARNINGS.

Local Irritation

Local irritation, erythema, mild pain, hematoma or ulceration may follow deep subcutaneous (intrafat) injection of heparin sodium. These complications are much more common after intramuscular use, and such use is not recommended.

Hypersensitivity

Generalized hypersensitivity reactions have been reported, with chills, fever and urticaria as the most usual manifestations, and asthma, rhinitis, lacrimation, headache, nausea and vomiting, and anaphylactoid reactions, including shock, occurring more rarely. Itching and burning, especially on the plantar side of the feet, may occur (see WARNINGS and PRECAUTIONS).

Certain episodes of painful, ischemic and cyanosed limbs have in the past been attributed to allergic vasospastic reactions. Whether these are in fact identical to the thrombocytopenia-associated complications, remains to be determined.

Miscellaneous

Osteoporosis following long-term administration of high doses of heparin, cutaneous necrosis after systemic administration, suppression of aldosterone synthesis, delayed transient alopecia, priapism, and rebound hyperlipemia on discontinuation of heparin sodium have also been reported.

Significant elevations of aminotransferase (SGOT [S-AST] and SGPT [S-ALT]) levels have occurred in a high percentage of patients (and healthy subjects) who have received heparin.

OVERDOSAGE

Symptoms

Bleeding is the chief sign of heparin overdosage. Nosebleeds, blood in urine or tarry stools may be noted as the first sign of bleeding. Easy bruising or petechial formations may precede frank bleeding.

Treatment

Neutralization of Heparin Effect—When clinical circumstances (bleeding) require reversal of heparinization, protamine sulfate (1% solution) by slow infusion will neutralize heparin sodium. No more than 50 mg should be administered, very slowly, in any 10 minute period. Each mg of protamine sulfate neutralizes approximately 100 USP heparin units. The amount of protamine required decreases over time as heparin is metabolized. Although the metabolism of heparin is complex, it may, for the purpose of choosing a protamine dose, be assumed to have a half-life of about 1/2 hour after intravenous injection.

Administration of protamine sulfate can cause severe hypotensive and anaphylactoid reactions. Because fatal reactions often resembling anaphylaxis have been reported, the drug should be given only when resuscitation techniques and treatment of anaphylactoid shock are readily available.

For additional information consult the labeling of Protamine Sulfate Injection, USP products.

DOSAGE AND ADMINISTRATION

Parenteral drug products should be inspected visually for particulate matter and discoloration prior to administration, whenever solution and container permit.

Confirm the choice of the correct Heparin Sodium Injection vial prior to administration of the drug to a patient (see WARNINGS, Fatal Medication Errors). The 1 mL vial must not be confused with a “catheter lock flush” vial or other 1 mL vial of inappropriate strength. Confirm that you have selected the correct medication and strength prior to administration of the drug.

When heparin is added to an infusion solution for continuous intravenous administration, the container should be inverted at least six times to ensure adequate mixing and prevent pooling of the heparin in the solution.

Heparin sodium is not effective by oral administration and should be given by intermittent intravenous injection, intravenous infusion, or deep subcutaneous (intrafat, i.e., above the iliac crest or abdominal fat layer) injection. The intramuscular route of administration should be avoided because of the frequent occurrence of hematoma at the injection site.

The dosage of heparin sodium should be adjusted according to the patient’s coagulation test results. When heparin is given by continuous intravenous infusion, the coagulation time should be determined approximately every four hours in the early stages of treatment. When the drug is administered intermittently by intravenous injection, coagulation tests should be performed before each injection during the early stages of treatment and at appropriate intervals thereafter. Dosage is considered adequate when the activated partial thromboplastin time (APTT) is 1.5 to 2 times normal or when the whole blood clotting time is elevated approximately 2.5 to 3 times the control value. After deep subcutaneous (intrafat) injections, tests for adequacy of dosage are best performed on samples drawn four to six hours after the injection.

Periodic platelet counts, hematocrits and tests for occult blood in stool are recommended during the entire course of heparin therapy, regardless of the route of administration.

Converting to Oral Anticoagulant

When an oral anticoagulant of the coumarin or similar type is to be begun in patients already receiving heparin sodium, baseline and subsequent tests of prothrombin activity must be determined at a time when heparin activity is too low to affect the prothrombin time. This is about five hours after the last IV bolus and 24 hours after the last subcutaneous dose. If continuous IV heparin infusion is used, prothrombin time can usually be measured at any time.

In converting from heparin to an oral anticoagulant, the dose of the oral anticoagulant should be the usual initial amount and thereafter prothrombin time should be determined at the usual intervals. To ensure continuous anticoagulation, it is advisable to continue full heparin therapy for several days after the prothrombin time has reached the therapeutic range. Heparin therapy may then be discontinued without tapering.

Therapeutic Anticoagulant Effect with Full-Dose Heparin

Although dosage must be adjusted for the individual patient according to the results of suitable laboratory tests, the following dosage schedules may be used as guidelines:

METHOD OF ADMINISTRATION | FREQUENCY | RECOMMENDED; DOSE (based on; 150 lb [68 kg] patient)
Deep Subcutaneous (Intrafat) Injection; A different site should be used for each injection to prevent the development of massive hematoma | Initial Dose | 5,000 units by IV injection, followed by 10,000 to 20,000 units of a concentrated solution, subcutaneously
Deep Subcutaneous (Intrafat) Injection; A different site should be used for each injection to prevent the development of massive hematoma | Every 8 hours | 8,000 to 10,000 units of a concentrated solution
Deep Subcutaneous (Intrafat) Injection; A different site should be used for each injection to prevent the development of massive hematoma | or; Every 12 hours | 15,000 to 20,000 units of a concentrated solution
Intermittent Intravenous Injection | Initial Dose | 10,000 units, either undiluted or in 50 to 100 mL of 0.9% Sodium Chloride Injection, USP
Intermittent Intravenous Injection | Every 4; to 6 hours | 5,000 to 10,000 units, either undiluted or in 50 to 100 mL of 0.9% Sodium Chloride Injection, USP
Intravenous Infusion | Initial Dose | 5,000 units by IV injection
Intravenous Infusion | Continuous | 20,000 to 40,000 units/24 hours in 1,000 mL of 0.9% Sodium Chloride Injection, USP (or in any compatible solution) for infusion

Pediatric Use

Use preservative-free HEPARIN SODIUM INJECTION in neonates and infants (see WARNINGS, Benzyl Alcohol Toxicity and PRECAUTIONS, Pediatric Use).

There are no adequate and well-controlled studies on heparin use in pediatric patients. Pediatric dosing recommendations are based on clinical experience. In general, the following dosage schedule may be used as a guideline in pediatric patients:

Initial Dose 75 to 100 units/kg (IV bolus over 10 minutes)

Maintenance Dose Infants: 25 to 30 units/kg/hour;

Infants < 2 months have the highest requirements

(average 28 units/kg/hour)

Children > 1 year of age: 18 to 20 units/kg/hour;

Older children may require less heparin, similar to weight-adjusted

adult dosage

Monitoring Adjust heparin to maintain aPTT of 60 to 85 seconds, assuming this

reflects an anti-Factor Xa level of 0.35 to 0.70.

Geriatric Use

Patients over 60 years of age may require lower doses of heparin.

Surgery of the Heart and Blood Vessels

Patients undergoing total body perfusion for open-heart surgery should receive an initial dose of not less than 150 units of heparin sodium per kilogram of body weight. Frequently, a dose of 300 units of heparin sodium per kilogram of body weight is used for procedures estimated to last less than 60 minutes, or 400 units per kilogram for those estimated to last longer than 60 minutes.

Low-Dose Prophylaxis of Postoperative Thromboembolism

A number of well-controlled clinical trials have demonstrated that low-dose heparin prophylaxis, given just prior to and after surgery, will reduce the incidence of postoperative deep vein thrombosis in the legs (as measured by the I-125 fibrinogen technique and venography) and of clinical pulmonary embolism. The most widely used dosage has been 5,000 units 2 hours before surgery and 5,000 units every 8 to 12 hours thereafter for seven days or until the patient is fully ambulatory, whichever is longer. The heparin is given by deep subcutaneous injection in the arm or abdomen with a fine needle (25 to 26 gauge) to minimize tissue trauma. A concentrated solution of heparin sodium is recommended. Such prophylaxis should be reserved for patients over the age of 40 who are undergoing major surgery. Patients with bleeding disorders and those having neurosurgery, spinal anesthesia, eye surgery or potentially sanguineous operations should be excluded, as well as patients receiving oral anticoagulants or platelet-active drugs (see WARNINGS). The value of such prophylaxis in hip surgery has not been established. The possibility of increased bleeding during surgery or postoperatively should be borne in mind. If such bleeding occurs, discontinuance of heparin and neutralization with protamine sulfate are advisable. If clinical evidence of thromboembolism develops despite low-dose prophylaxis, full therapeutic doses of anticoagulants should be given unless contraindicated. All patients should be screened prior to heparinization to rule out bleeding disorders, and monitoring should be performed with appropriate coagulation tests just prior to surgery. Coagulation test values should be normal or only slightly elevated. There is usually no need for daily monitoring of the effect of low-dose heparin in patients with normal coagulation parameters.

Extracorporeal Dialysis

Follow equipment manufacturers’ operating directions carefully.

Blood Transfusion

Addition of 400 to 600 USP units per 100 mL of whole blood is usually employed to prevent coagulation. Usually, 7,500 USP units of heparin sodium are added to 100 mL of 0.9% Sodium Chloride Injection, USP (or 75,000 USP units/1,000 mL of 0.9% Sodium Chloride Injection, USP) and mixed; from this sterile solution, 6 to 8 mL are added per 100 mL of whole blood.

Laboratory Samples

Addition of 70 to 150 units of heparin sodium per 10 to 20 mL sample of whole blood is usually employed to prevent coagulation of the sample. Leukocyte counts should be performed on heparinized blood within two hours after addition of the heparin. Heparinized blood should not be used for isoagglutinin, complement, or erythrocyte fragility tests or platelet counts.

HOW SUPPLIED

Heparin Sodium Injection, USP (porcine), preservative free, is available as follows:

Product; No. | NDC; No. | Strength | Fill Volume
27602 | 63323-276-02 | 2,000 USP Heparin units per 2 mL; (1,000 USP Heparin units per mL) | 2 mL fill in a 2 mL single dose, flip-top vial, in packages of 25.
504302 | 63323-543-02 | 5,000 USP Heparin units per 0.5 mL | 0.5 mL fill in a 2 mL single dose, flip-top vial, in packages of 25.

Use only if solution is clear and seal intact. Do not use if solution is discolored or contains a precipitate. Discard unused portion.

This container closure is not made from natural rubber latex.

Heparin Sodium Injection, USP (porcine) contains benzyl alcohol and is available as follows:

Product No. | NDC; No. | Strength | Fill Volume
4710 | 63323-047-10 | 50,000 USP Heparin units per 10 mL; (5,000 USP Heparin units per mL) | 10 mL fill in a 10 mL multi-dose, flip-top vial, in packages of 25.
504509 | 63323-459-09 | 40,000 USP Heparin units per 4 mL; (10,000 USP Heparin units per mL) | 4 mL fill in a 5 mL multi-dose, flip-top vial, in packages of 25.

Use only if solution is clear and seal intact. Do not use if solution is discolored or contains a precipitate.

This container closure is not made from natural rubber latex.

Heparin Sodium Injection, USP (porcine) contains parabens and is available in multi-dose, flip-top vials, in packages of 25, as follows:

Product; No. | NDC; No. | Strength | Fill Volume
504001* | 63323-540-01 | 1,000 USP Heparin units per 1 mL | 1 mL fill in a 3 mL vial.
504011 | 63323-540-11 | 10,000 USP Heparin units per 10 mL; (1,000 USP Heparin units per mL) | 10 mL fill in a 10 mL vial.
504031 | 63323-540-31 | 30,000 USP Heparin units per 30 mL; (1,000 USP Heparin units per mL) | 30 mL fill in a 30 mL vial.
926201** | 63323-262-01 | 5,000 USP Heparin units per 1 mL | 1 mL fill in a 3 mL vial.
504201* | 63323-542-01 | 10,000 USP Heparin units per 1 mL | 1 mL fill in a 3 mL vial.
504207 | 63323-542-07 | 50,000 USP Heparin units per 5 mL; (10,000 USP Heparin units per mL) | 5 mL fill in a 6 mL vial.
915501** | 63323-915-01 | 20,000 USP Heparin units per 1 mL | 1 mL fill in a 3 mL vial.

*Packaged in a plastic or glass vial.

**Packaged in a plastic vial.

Use only if solution is clear and seal intact. Do not use if solution is discolored or contains a precipitate.

This container closure is not made from natural rubber latex.

STORAGE

Store at 20° to 25°C (68° to 77°F) [see USP Controlled Room Temperature].

REFERENCES

1. Tahata T, Shigehito M, Kusuhara K, Ueda Y, et al. Delayed-Onset of Heparin Induced Thrombocytopenia – A Case Report – J Jpn Assn Torca Surg. 1992;40(3):110-111.
2. Warkentin T, Kelton J. Delayed-Onset Heparin-Induced Thrombocytopenia and Thrombosis. Annals of Internal Medicine. 2001;135:502-506.
3. Rice L, Attisha W, Drexler A, Francis J. Delayed-Onset Heparin Induced Thrombocytopenia. Annals of Internal Medicine, 2002;136:210-215.
4. Dieck J., C. Rizo-Patron, et al. (1990). “A New Manifestation and Treatment Alternative for Heparin-Induced Thrombosis.” Chest 98(1524-26).
5. Smythe M, Stephens J, Mattson. Delayed-Onset Heparin Induced Thrombocytopenia. Annals of Emergency Medicine, 2005;45(4):417-419.
6. Divgi A. (Reprint), Thumma S., Hari P., Friedman K. Delayed Onset Heparin-Induced Thrombocytopenia (HIT) Presenting After Undocumented Drug Exposure as Post-Angiography Pulmonary Embolism. Blood. 2003;102(11):127b.

For Product Inquiry: 1-800-551-7176

451209F

Revised: March 2014

PACKAGE LABEL

PACKAGE LABEL - PRINCIPAL DISPLAY PANEL - Heparin 1 mL Multi-Dose Vial Label

Not for Lock Flush

Heparin Sodium Injection, USP

1,000 USP units per mL

For intravenous or subcutaneous use

1 mL

PACKAGE LABEL - PRINCIPAL DISPLAY PANEL - Heparin 1 mL Multi-Dose Vial Tray Label

NDC 63323-540-01

Heparin Sodium Injection, USP

1,000 USP units per mL

For intravenous or subcutaneous use

1 mL

PACKAGE LABEL - PRINCIPAL DISPLAY PANEL - Heparin 1 mL Multi-Dose Vial Label

Not for Lock Flush

Heparin Sodium Injection, USP

5,000 USP units per mL

For intravenous or subcutaneous use

1 mL

PACKAGE LABEL - PRINCIPAL DISPLAY PANEL - Heparin 1 mL Multi-Dose Vial Tray Label

NDC 63323-262-01

Heparin Sodium Injection, USP

5,000 USP units per mL

For intravenous or subcutaneous use

1 mL

PACKAGE LABEL - PRINCIPAL DISPLAY PANEL - Heparin 1 mL Multi-Dose Vial Label

Not for Lock Flush

Heparin Sodium Injection, USP

10,000 USP units per mL

For intravenous or subcutaneous use

1 mL

PACKAGE LABEL - PRINCIPAL DISPLAY PANEL - Heparin 1 mL Multi-Dose Vial Tray Label

NDC 63323-542-01

Heparin Sodium Injection, USP

10,000 USP units per mL

For intravenous or subcutaneous use

1 mL

PACKAGE LABEL - PRINCIPAL DISPLAY PANEL - Heparin 4 mL Multi-Dose Vial Label

Heparin Sodium Injection, USP

40,000 USP units per 4 mL (10,000 USP units per mL)

For intravenous or subcutaneous use

PACKAGE LABEL - PRINCIPAL DISPLAY PANEL - Heparin 4 mL Multi-Dose Vial Tray Label

NDC 63323-459-09

Heparin Sodium Injection, USP

40,000 USP units per 4 mL (10,000 USP units per mL)

For intravenous or subcutaneous use

PACKAGE LABEL - PRINCIPAL DISPLAY PANEL - Heparin 1 mL Multi-Dose Vial Label

Not for Lock Flush

Heparin Sodium Injection, USP

20,000 USP units per mL

For intravenous or subcutaneous use

1 mL

PACKAGE LABEL - PRINCIPAL DISPLAY PANEL - Heparin 1 mL Multi-Dose Vial Tray Label

NDC 63323-915-01

Heparin Sodium Injection, USP

20,000 USP units per mL

For intravenous or subcutaneous use

1 mL

PACKAGE LABEL - PRINCIPAL DISPLAY PANEL - Heparin 2 mL Single Dose Vial Label

Not for Lock Flush

NDC 63323-276-01 27602

Heparin Sodium Injection, USP

2,000 USP units per 2 mL (1,000 USP units per mL)

For IV or SC use

Preservative Free

PACKAGE LABEL - PRINCIPAL DISPLAY PANEL - Heparin 2 mL Single Dose Vial Tray Label

NDC 63323-276-02 27602

Heparin Sodium Injection, USP

2,000 USP units per 2 mL (1,000 USP units per mL)

For IV or SC use

Preservative Free

25 Vials

PACKAGE LABEL - PRINCIPAL DISPLAY PANEL - Heparin 10 mL Multi-Dose Vial Label

NDC 63323-047-01 4710

Heparin Sodium Injection, USP

50,000 USP units per 10 mL (5,000 USP units per mL)

For intravenous or subcutaneous use

PACKAGE LABEL - PRINCIPAL DISPLAY PANEL - Heparin 10 mL Multi-Dose Tray Label

NDC 63323-047-10 4710

Heparin Sodium Injection, USP

50,000 USP units per 10 mL (5,000 USP units per mL)

For intravenous or subcutaneous use

25 Vials

PACKAGE LABEL - PRINCIPAL DISPLAY PANEL - Heparin 0.5 mL Single Dose Vial Label

Not for Lock Flush

Heparin Sodium Injection, USP

5,000 USP units per 0.5 mL

For IV or SC use

Preservative Free

PACKAGE LABEL - PRINCIPAL DISPLAY PANEL - Heparin 0.5 mL Single Dose Vial Tray Label

NDC 63323-543-02

Heparin Sodium Injection, USP

5,000 USP units per 0.5 mL

For intravenous or subcutaneous use

Preservative Free